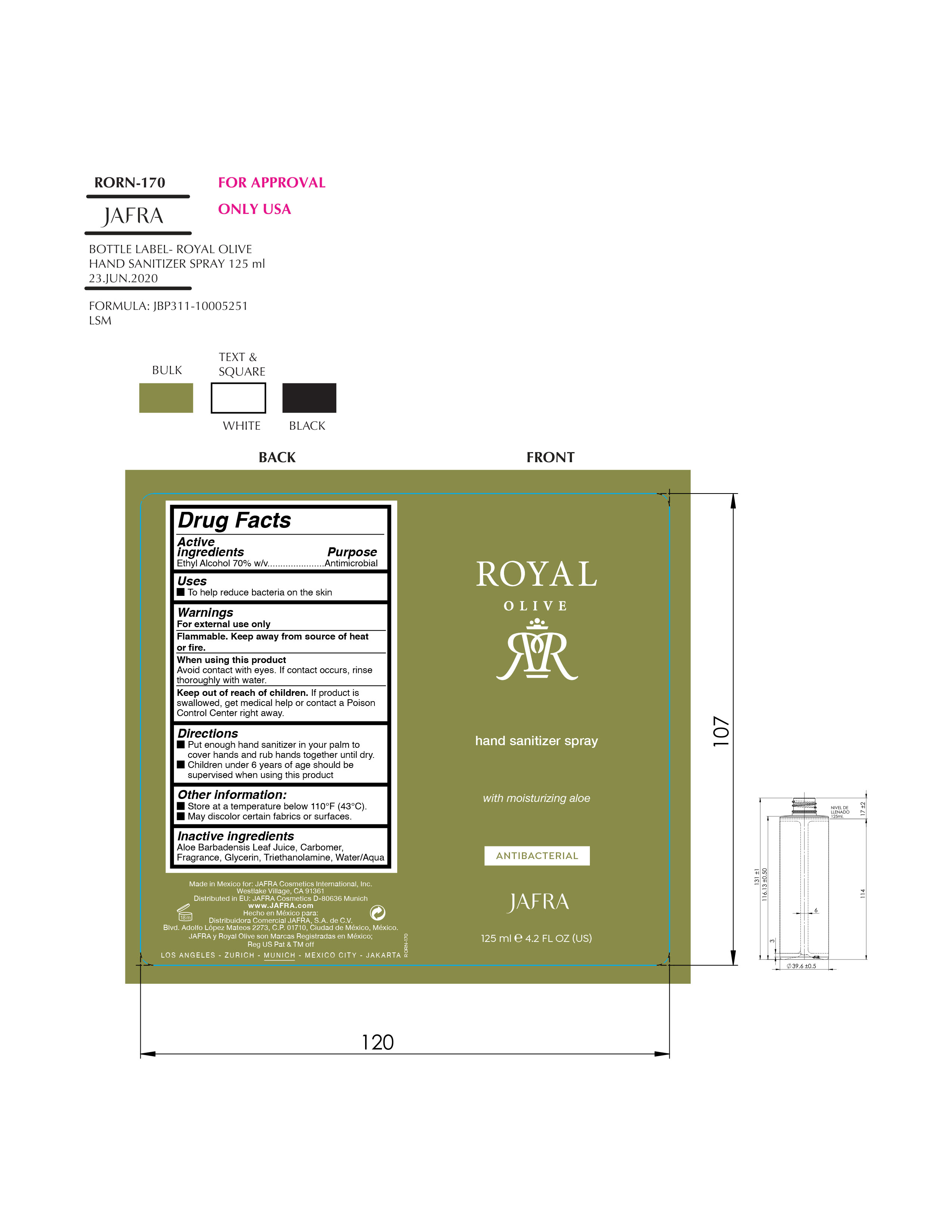 DRUG LABEL: Royal Olive Hand Sanitizer
NDC: 68828-107 | Form: SPRAY
Manufacturer: Jafra Cosmetics International Inc
Category: otc | Type: HUMAN OTC DRUG LABEL
Date: 20200630

ACTIVE INGREDIENTS: ALCOHOL 70 mL/100 mL
INACTIVE INGREDIENTS: TROLAMINE; GLYCERIN; ALOE VERA LEAF; WATER; CARBOMER HOMOPOLYMER, UNSPECIFIED TYPE

Royal Olive Hand Sanitizer Spray

Active Ingredient(s)

Alcohol 70% v/v. Purpose: Antiseptic

Uses

to help reduce bacteria that potentially can cause disease. For use when soap and water are not available.

Keep out of reach of children. If swallowed, get medical help or contact a Poison Control Center right away.

Warnings

For external use only.

Flammable. Keep away from heat or flame

When using this product keep out of eyes, ears, and mouth. In case of contact with eyes, rinse eyes thoroughly with water.

when using this product

Avoid contact with eyes. If contact occurs, rinse thouroughly with water.

Directions

- Put enough hand Sanitizer in your palm to cover hands rub hands together until dry.
- Children under 6 years of age should be supervised when using this product

Other information

- Store at temperaturebelow 110F
- Avoid freezing and excessive heat above 40C (104F)

Inactive ingredients

Aloe Barbadensis Leaf Juice, Carbomer, Fragrance, Glycerin, Triethanolamine, Water/Aqua

PACKAGE LABEL

Royal Olive hand Sanitizer spray

with moisturizing aloe

Antibacterial

Jafra

125ml 4.2 FL OZ (US)